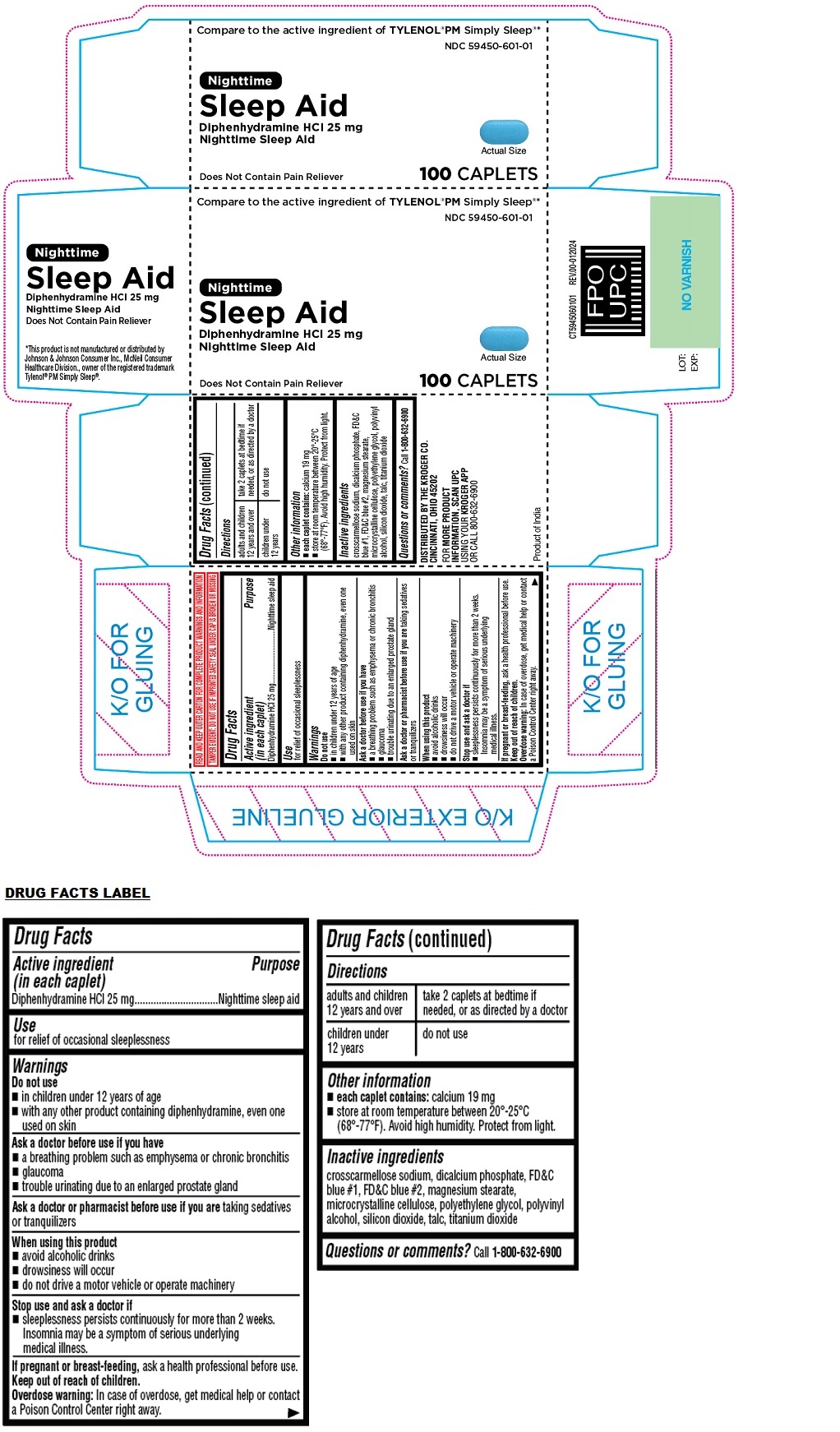 DRUG LABEL: Kroger Nighttime Sleep Aid CAPLET
NDC: 59450-601 | Form: TABLET, FILM COATED
Manufacturer: The Kroger Co.
Category: otc | Type: HUMAN OTC DRUG LABEL
Date: 20240129

ACTIVE INGREDIENTS: DIPHENHYDRAMINE HYDROCHLORIDE 25 mg/1 1
INACTIVE INGREDIENTS: CROSCARMELLOSE SODIUM; ANHYDROUS DIBASIC CALCIUM PHOSPHATE; FD&C BLUE NO. 1; FD&C BLUE NO. 2; MAGNESIUM STEARATE; MICROCRYSTALLINE CELLULOSE; POLYETHYLENE GLYCOL, UNSPECIFIED; POLYVINYL ALCOHOL, UNSPECIFIED; SILICON DIOXIDE; TALC; TITANIUM DIOXIDE

Nighttime Sleep Aid CAPLET

Active ingredient (in each caplet)

Diphenhydramine HCl 25 mg

Purpose

Nighttime sleep aid

Use

for relief of occasional sleeplessness

Warnings

Do not use
• in children under 12 years of age
• with any other product containing diphenhydramine, even one used on skin

Ask a doctor before use if you have
• a breathing problem such as emphysema or chronic bronchitis
• glaucoma
• trouble urinating due to an enlarged prostate gland

Ask a doctor or pharmacist before use if you are taking sedatives or tranquilizers

When using this product
• avoid alcoholic drinks
• drowsiness will occur
• do not drive a motor vehicle or operate machinery

Stop use and ask a doctor if
• sleeplessness persists continuously for more than 2 weeks. Insomnia may be a symptom of serious underlying medical illness.

If pregnant or breast-feeding, ask a health professional before use.

Keep out of reach of children.
Overdose warning: In case of overdose, get medical help or contact a Poison Control Center right away.

Directions

adults and children 12 years and over | take 2 caplets at bedtime if needed, or as directed by a doctor
children under 12 years | do not use

Other information

• each caplet contains: calcium 19 mg
• store at room temperature between 20°-25°C (68°-77°F). Avoid high humidity. Protect from light.

Inactive ingredients

croscarmellose sodium, dicalcium phosphate, FD&C blue #1, FD&C blue #2, magnesium stearate, microcrystalline cellulose, polyethylene glycol, polyvinyl alcohol, silicon dioxide, talc, titanium dioxide

Questions or comments?

call 1-800-632-6900

Compare to the active ingredient of TYLENOL® PM Simply Sleep®*

Does Not Contain Pain Reliever

READ AND KEEP OUTER CARTON FOR COMPLETE PRODUCT WARNINGS AND INFORMATION

TAMPER EVIDENT: DO NOT USE IF IMPRINTED SAFETY SEAL UNDER CAP IS BROKEN OR MISSING

DISTRIBUTED BY THE KROGER CO.
CINCINNATI, OHIO 45202

FOR MORE PRODUCT INFORMATION, SCAN UPC USING YOUR KROGER APP OR CALL 800-632-6900

Product of India

*This product is not manufactured or distributed by Johnson & Johnson Consumer Inc. McNeil Consumer Healthcare Division., owner of the registered trademark Tylenol® PM Simply Sleep®.